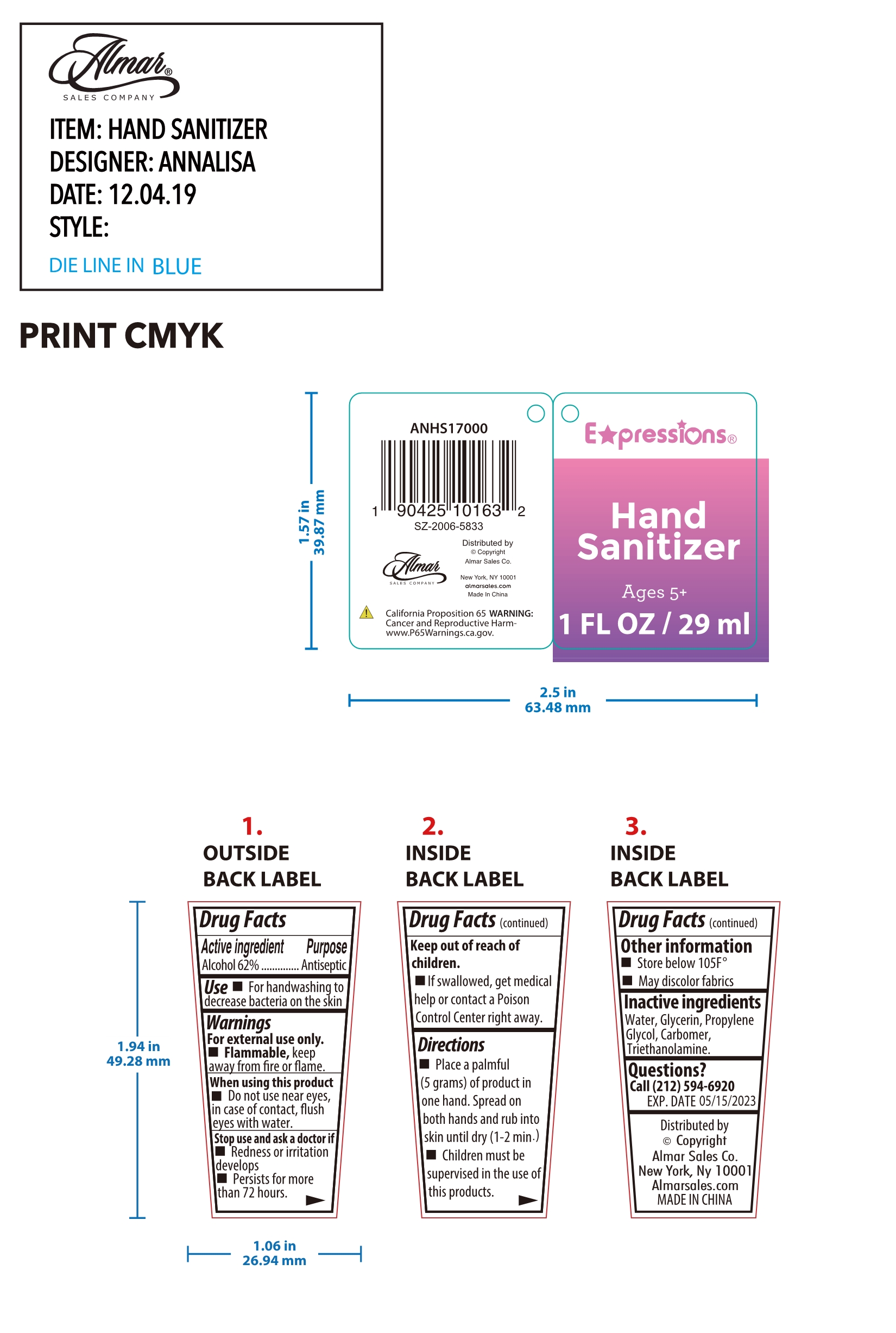 DRUG LABEL: Hand Sanitizer
NDC: 79867-001 | Form: GEL
Manufacturer: Guangzhou meizi biotechnology co. LTD
Category: otc | Type: HUMAN OTC DRUG LABEL
Date: 20220330

ACTIVE INGREDIENTS: ALCOHOL 62 mL/100 mL
INACTIVE INGREDIENTS: CARBOMER HOMOPOLYMER, UNSPECIFIED TYPE; GLYCERIN; WATER; PROPYLENE GLYCOL; TROLAMINE

Hand Sanitizer

Active Ingredient(s)

Alcohol 62%

Purpose

Antiseptic

Use

For handwashing to decrease bacteria on the skin

Warnings

For external use only.
Flammable keep away from fre or flame.

Do not use near eyes,in case of contact flush eyes with water

Do not use near eyes,in case of contact flush eyes with water

STOP USE

Redness or irritationdevelops
Persists for morehan 72 hours

KEEP OUT OF REACH OF CHILDREN

If swallowed, get medical help or contact a Poison Control Center right away

Directions

Place a palmful (5 grams)of product in one hand. spread on both hands and rub into skin until dry (1-2 min）
Children must be supervised in the use of this products.

Other information

Store below105F°
May discolor fabrics

Inactive ingredients

Water, Glycerin, Propylene Glycol, carbomer, Triethanolamine